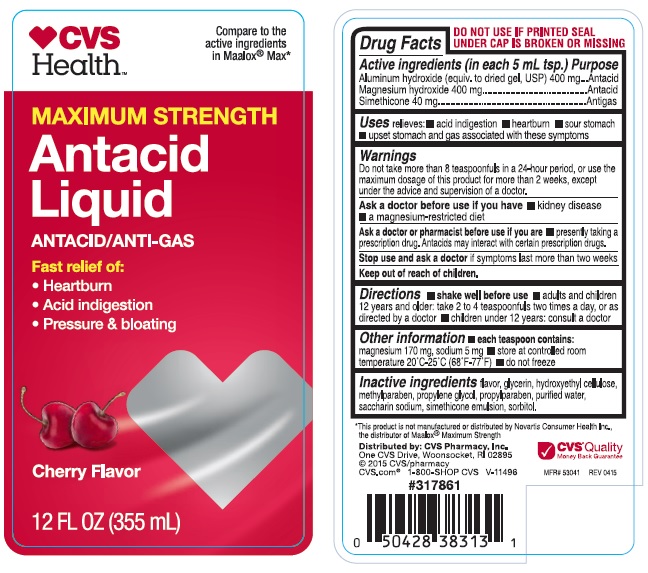 DRUG LABEL: Antacid
NDC: 69842-508 | Form: SUSPENSION
Manufacturer: CVS
Category: otc | Type: HUMAN OTC DRUG LABEL
Date: 20170809

ACTIVE INGREDIENTS: ALUMINUM HYDROXIDE 400 mg/5 mL; MAGNESIUM HYDROXIDE 400 mg/5 mL; DIMETHICONE 40 mg/5 mL
INACTIVE INGREDIENTS: GLYCERIN; HYDROXYETHYL CELLULOSE (100 MPA.S AT 2%); METHYLPARABEN; PROPYLPARABEN; WATER; SACCHARIN SODIUM; SORBITOL

CVS Maximum Strength Antacid Liquid

Active ingredient (in each 5mL tsp.)

Aluminum hydroxide (equvi. to dried gel, USP) 400 mg

Magnesium hydroxide 400 mg

Simethicone 40 mg

Purpose

Antacid

Antacid

Antigas

Uses

- relieves:
- acid indigestion
- heartburn
- sour stomach
- upset stomach and gas associated with these symptoms

Warnings

Do not take more than 8 teaspoonfuls in a 24-hour period, or use the maximum dosage of this product for more than 2 weeks, except under the advice and supervision of a doctor.

Ask a doctor before use if you have

- kidney disease
- a magnesium-restricted diet

Ask a doctor or pharmacist before use if you are

- presently taking a prescription drug. Antacids may interact with certain prescription drugs.

Stop use and ask a doctor

if symptoms last more than two weeks

Directions

- shake well before use.
- adults and children 12 years and older: take 2 to 4 teaspoonfuls two times a day, or as directed by a doctor
- children under 12 years: consult a doctor

Other information

- each teaspoon contains: magnesium 170 mg, sodium 5 mg
- store at controlled room temperature 20oC-25oC (68oF-77oF)
- do not freeze

Inactive ingredients

flavor, glycerin, hydroxyethylcellulose, methylparaben, propylene glycol, purified water, saccharin sodium, simethicone emulsion, sorbitol

PDP

Compare to the active ingredients in Maalox max

Maximum strength Antacid Liquid

Antacid / Anti-gas

Fast relief of:

Heartburn

Acid indigestion

Pressure & Bloating

Cherry Flavor

12 FL OZ (355 mL)